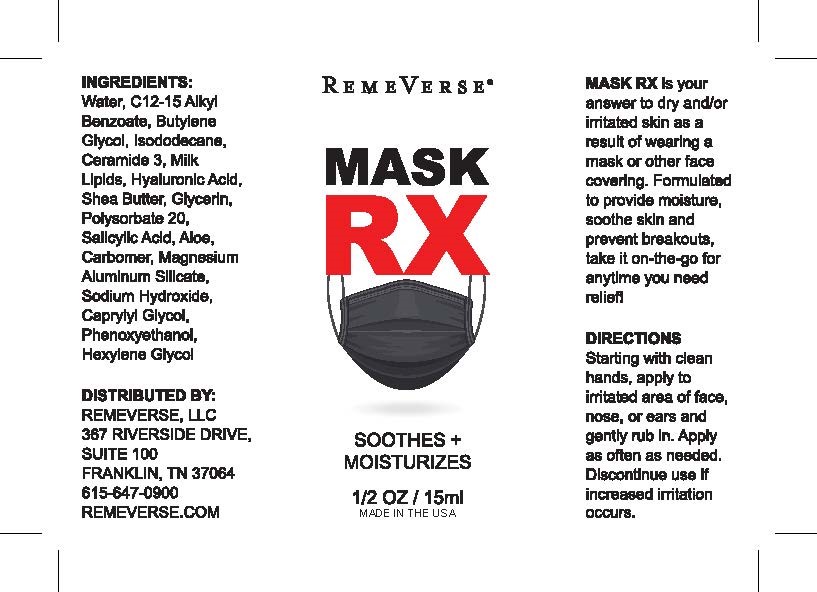 DRUG LABEL: Mask RX
NDC: 70317-004 | Form: CREAM
Manufacturer: Remeverse
Category: otc | Type: HUMAN OTC DRUG LABEL
Date: 20241216

ACTIVE INGREDIENTS: SALICYLIC ACID 0.225 g/15 g
INACTIVE INGREDIENTS: CERAMIDE 3; POLYSORBATE 20; ALOE; C12-15 ALKYL LACTATE; HEXYLENE GLYCOL; CAPRYLYL GLYCOL; HYALURONIC ACID; SHEA BUTTER; MAGNESIUM ALUMINUM SILICATE; GLYCERIN; WATER; SODIUM HYDROXIDE; PHENOXYETHANOL; ISODODECANE

Mask RX

Mask RX Active ingredients

Salicylic Acid

Inactive Ingredients

Water, C12-15 Alkyl Benzoate, Butylene Glycol, Isodocecane, Ceramide 3, Milk Lipids, Hyaluronic Acid, Shea Butter, Glycerin, Polysorbate 20, Aloe, Carbomer, Magnesium Aluminum Silicate, Sodium Hydroxide, Caprylyl Glycol, Phenoxyethanol, Hexylene Glycol

Directions

Starting with clean hands, apply to irritated area of face, nose, or ears and gently rub in. Apply as often as needed. Discontinue use if increased irritation occurs.

Use

For treatment of acne

Stop use section

Sensitivity test for a new user. Apply product sparingly to one or two small affected areas during the first 3 days. If no discomfor occurs, follow the directions stated above.

Warnings

For external use only

Do not use this medication if you have very sensiteive skin - are sensitive to Salicylic Acid.

Ask a doctor or a pharmacist before use if you are using other topical acne medications at the same time or immediately following use of this product.

When using this product - Avoid unnecessary sun exposure and use a sunscreen - Avoid contact with eyes, lips and mouth. - Skin irritation and dryness is more likely to occur if you use another topical acne medication at a time. Avoid contact with hair and dyed fabrics, which may be reduced by using this product less frequently or in a lower concentration.

Stop use and ask a doctor if skin irritation becomes severe.

Mask RX

For treatment of Acne

Warning - keep out of the reach of children.

Keep out of the reach of children. If swallowed, get medical help or contact a Poison Control Center right away.